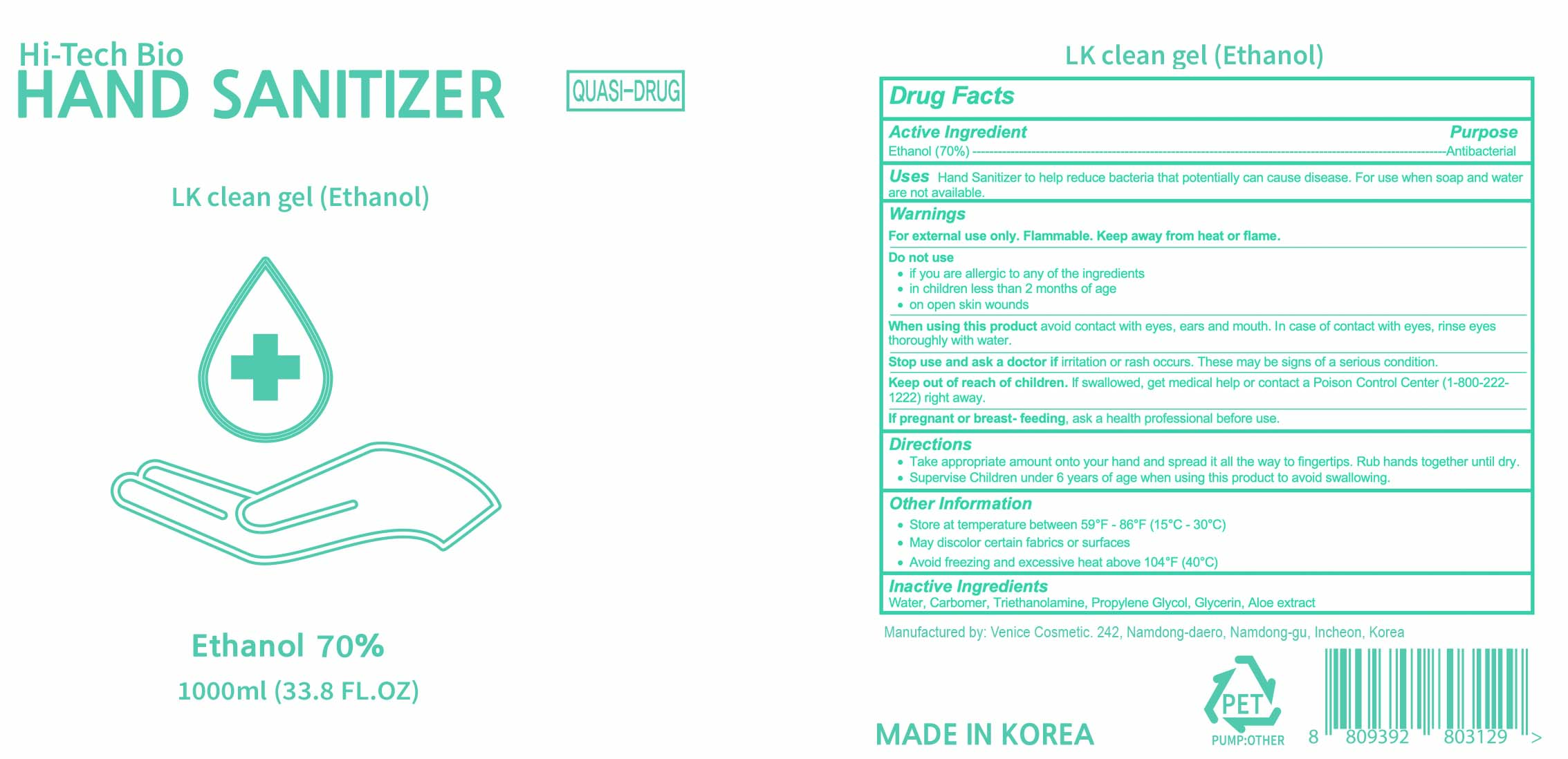 DRUG LABEL: LK clean gel (Ethanol)
NDC: 74488-009 | Form: GEL
Manufacturer: Venice Cosmetic
Category: otc | Type: HUMAN OTC DRUG LABEL
Date: 20200513

ACTIVE INGREDIENTS: ALCOHOL 70 mL/100 mL
INACTIVE INGREDIENTS: GLYCERIN; TROLAMINE; WATER; CARBOMER HOMOPOLYMER, UNSPECIFIED TYPE; PROPYLENE GLYCOL; ALOE

LK clean gel (Ethanol)

Active ingredient

Ethanol 70%

Uses

Hand sanitizer for decreasing bacteria on skin

Purpose

Antibacterial

Warnings

For external use only

Do not use if you are allergic to any of the ingredients

When using this product avoid contact with eyes. If contact occurs, rinse eyes thoroughly with water. avoid contact with broken, irritated, or itching skin. Do not puncture or incinerate.

Stop use and ask a doctor if irritation or redness develops and condition persists for more than 72 hours

If pregnant or breast-feeding, ask a health professional before use.

Directions

Take appropriate amount onto your hand and spread it all the way to fingertips. Rub the contents until it dries

Inactive ingredients

Water, Carbomer, Triethanolamine, Propylene Glycol, Glycerin, Aloe Extract

Keep out of reach of children. If swallowed, get medical help or contact a Poison Control Center (1-800-222-1222) right away.